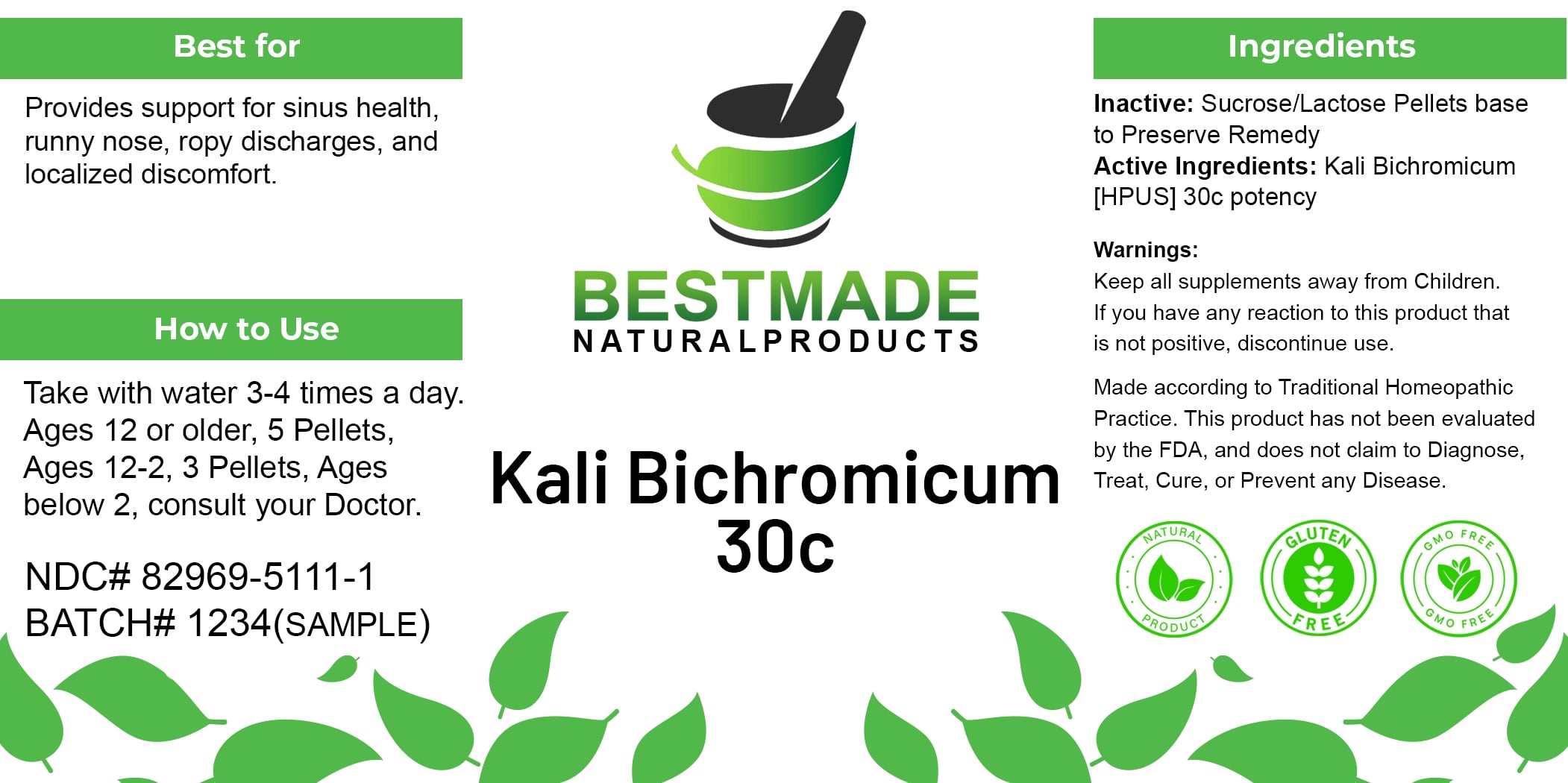 DRUG LABEL: Bestmade Natural Products Kali Bichromicum
NDC: 82969-5111 | Form: TABLET, SOLUBLE
Manufacturer: Bestmade Natural Products
Category: homeopathic | Type: HUMAN OTC DRUG LABEL
Date: 20241219

ACTIVE INGREDIENTS: POTASSIUM DICHROMATE 30 [hp_C]/30 [hp_C]
INACTIVE INGREDIENTS: LACTOSE 30 [hp_C]/30 [hp_C]; SUCROSE 30 [hp_C]/30 [hp_C]

KALI BICHROMICUM 30C

DOSAGE AND ADMINISTRATION

Take with water 3-4 times a day
Ages 12 or older, 5 Pellets, Ages 12-2, 3 Pellets, Ages below 2, consult your Doctor.

INDICATIONS AND USAGE

Best for

Provides support for sinus health, runny nose, ropy discharges, and localized discomfort

Inactive: Sucrose/Lactose Pellets base to Preserve Remedy

Active Ingredients: Kali Bichromicum [HPUS] 30c potency

Warnings:

Keep all supplements away from Children.

If you have any reaction to this product that is not positive, discontinue use.

Made according to Traditional Homeopathic Practice. This product has not been evaluated by the FDA, and does not claim to Diagnose, Treat, Cure, or Prevent any Disease.

PURPOSE

Best for

Provides support for sinus health, runny nose, ropy discharges, and localized discomfort

Warnings:

Keep all supplements away from Children.

If you have any reaction to this product that is not positive, discontinue use.

Made according to Traditional Homeopathic Practice. This product has not been evaluated by the FDA, and does not claim to Diagnose, Treat, Cure, or Prevent any Disease.

Entire package label